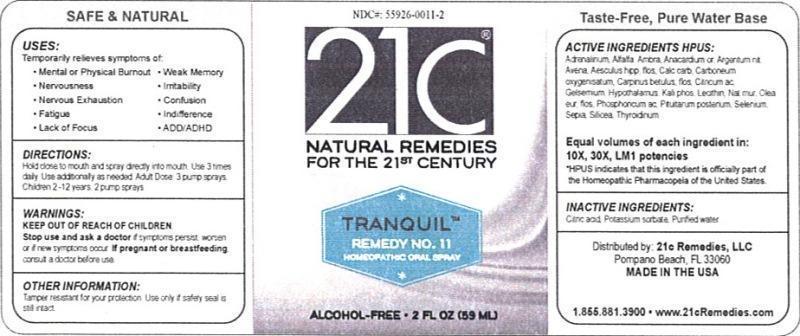 DRUG LABEL: Tranquil Remedy No. 11
NDC: 55926-0011 | Form: LIQUID
Manufacturer: Speer Laboratories, LLC
Category: homeopathic | Type: HUMAN OTC DRUG LABEL
Date: 20130801

ACTIVE INGREDIENTS: EPINEPHRINE 10 [hp_X]/59 mL; ALFALFA 10 [hp_X]/59 mL; AMBROSIA ARTEMISIIFOLIA 10 [hp_X]/59 mL; SEMECARPUS ANACARDIUM JUICE 10 [hp_X]/59 mL; SILVER NITRATE 10 [hp_X]/59 mL; AVENA SATIVA FLOWERING TOP 10 [hp_X]/59 mL; AESCULUS HIPPOCASTANUM FLOWER 10 [hp_X]/59 mL; OYSTER SHELL CALCIUM CARBONATE, CRUDE 10 [hp_X]/59 mL; CARBON MONOXIDE 10 [hp_X]/59 mL; CARPINUS BETULUS FLOWERING TOP 10 [hp_X]/59 mL; ANHYDROUS CITRIC ACID 10 [hp_X]/59 mL; GELSEMIUM SEMPERVIRENS ROOT 10 [hp_X]/59 mL; BOS TAURUS HYPOTHALAMUS 10 [hp_X]/59 mL; POTASSIUM PHOSPHATE, DIBASIC 10 [hp_X]/59 mL; EGG PHOSPHOLIPIDS 10 [hp_X]/59 mL; SODIUM CHLORIDE 10 [hp_X]/59 mL; OLEA EUROPAEA FLOWER 10 [hp_X]/59 mL; PHOSPHORIC ACID 10 [hp_X]/59 mL; SUS SCROFA PITUITARY GLAND 10 [hp_X]/59 mL; SELENIUM 10 [hp_X]/59 mL; SEPIA OFFICINALIS JUICE 10 [hp_X]/59 mL; SILICON DIOXIDE 10 [hp_X]/59 mL; THYROID, UNSPECIFIED 10 [hp_X]/59 mL
INACTIVE INGREDIENTS: CITRIC ACID MONOHYDRATE; POTASSIUM SORBATE; WATER

Tranquil Remedy No. 11

ACTIVE INGREDIENT

Active Ingredients HPUS: Adrenalinum, Alfalfa, Ambrosia artemisiaefolia, Anacardium orientale, Argentum nitricum, Avena sativa, Aesculus hippocastanum, flos, Calcarea carbonica, Carboneum oxygenisatum, Carpinus betulus, flos, Citricum acidum, Gelsemium sempervirens, Hypothalamus, Kali phosphoricum, Lecithin, Natrum muriaticum, Olea europaea, flos, Phosphoricum acidum, Pituitarum posterium, Selenium metallicum, Sepia, Silicea, Thyroidinum.

Equal volumes of each ingredient in: 10X, 30X, LM1 potencies.

HPUS indicates that this ingredient is officially part of the Homeopathic Pharmacopeia of the United States.

Inactive Ingredients: Citric acid, Potassium sorbate, Purified water.

INDICATIONS AND USAGE

Uses: Temporarily relieves symptoms of:

- mental or physical burnout
- nervousness
- nervous exhaustion
- fatigue
- lack of focus
- weak memory
- irritability
- confusion
- indifference
- ADD/ADHD

Directions:

Hold close to mouth and spray directly into mouth. Use 3 times daily. Use additionally as needed. Adult dose: 3 pump sprays. Children 2-12 years: 2 pump sprays.

Keep out of reach of children.

WARNINGS

Warnings: Stop use and ask a doctor if symptoms persist, worsen or if new symptoms occur. If pregnant or breastfeeding, consult a doctor before use.

OTHER SAFETY INFORMATION

Tamper resistant for your protection. Use only if safety seal is still intact.

PURPOSE

Uses: Temporarily relieves symptoms of: mental or physical burnout, nervousness, nervous exhaustion, fatigue, lack of focus, weak memory, irritability, confusion, indifference, ADD/ADHD.